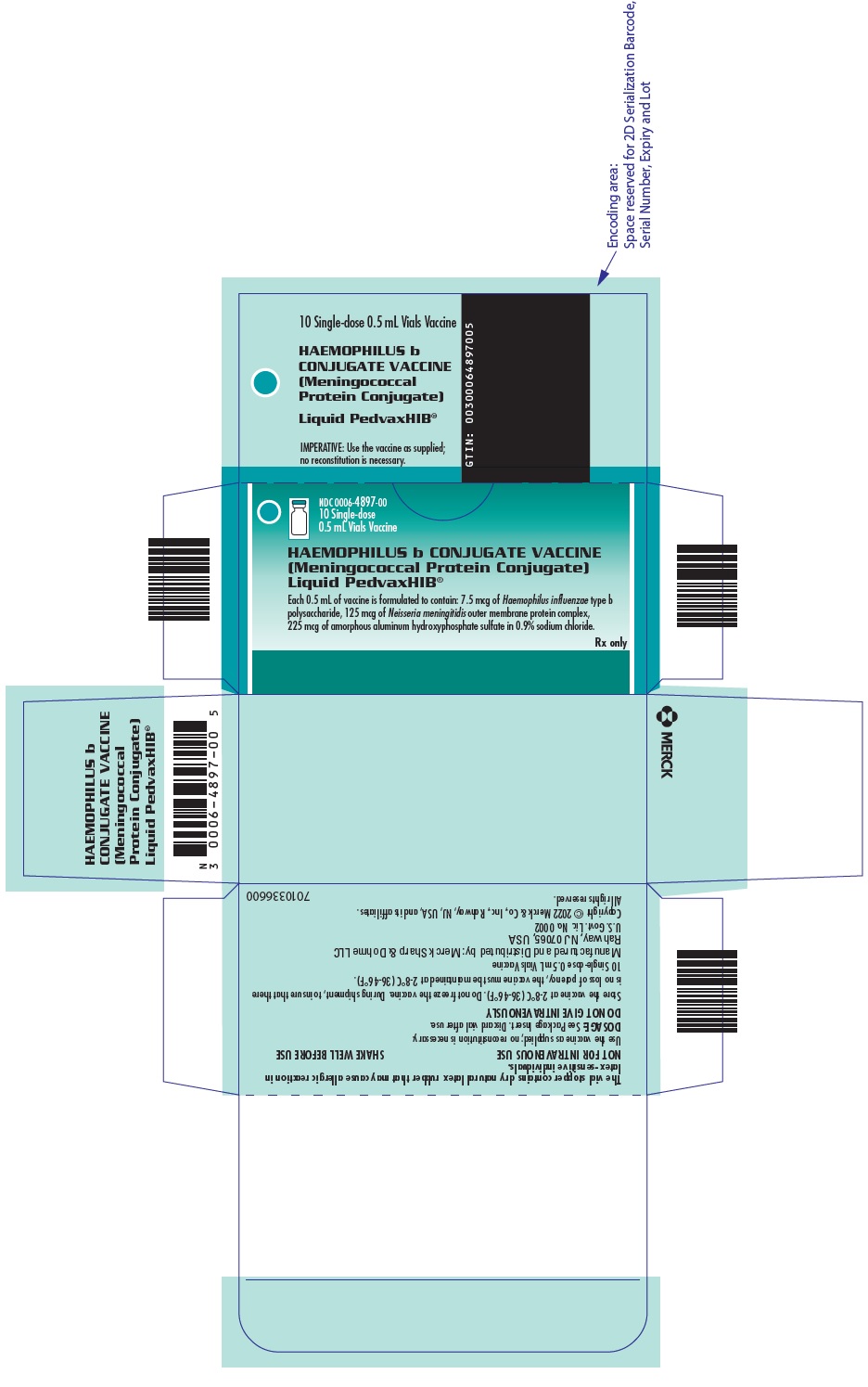 DRUG LABEL: PedvaxHIB
NDC: 0006-4897 | Form: INJECTION, SUSPENSION
Manufacturer: Merck Sharp & Dohme LLC
Category: other | Type: VACCINE LABEL
Date: 20241022

ACTIVE INGREDIENTS: HAEMOPHILUS INFLUENZAE TYPE B CAPSULAR POLYSACCHARIDE MENINGOCOCCAL OUTER MEMBRANE PROTEIN CONJUGATE ANTIGEN 7.5 ug/0.5 mL
INACTIVE INGREDIENTS: SODIUM CHLORIDE

PedvaxHIB® Liquid
[Haemophilus b Conjugate Vaccine
(Meningococcal Protein Conjugate)]

DESCRIPTION

PedvaxHIB® [Haemophilus b Conjugate Vaccine (Meningococcal Protein Conjugate)] is a highly purified capsular polysaccharide (polyribosylribitol phosphate or PRP) of Haemophilus influenzae type b (Haemophilus b, Ross strain) that is covalently bound to an outer membrane protein complex (OMPC) of the B11 strain of Neisseria meningitidis serogroup B. The covalent bonding of the PRP to the OMPC which is necessary for enhanced immunogenicity of the PRP is confirmed by quantitative analysis of the conjugate's components following chemical treatment which yields a unique amino acid. The potency of PedvaxHIB is determined by assay of PRP.

Haemophilus influenzae type b and Neisseria meningitidis serogroup B are grown in complex fermentation media. The PRP is purified from the culture broth by purification procedures which include ethanol fractionation, enzyme digestion, phenol extraction and diafiltration. The OMPC from Neisseria meningitidis is purified by detergent extraction, ultracentrifugation, diafiltration and sterile filtration.

Liquid PedvaxHIB is ready to use and does not require a diluent. Each 0.5 mL dose of Liquid PedvaxHIB is a sterile product formulated to contain: 7.5 mcg of Haemophilus b PRP, 125 mcg of Neisseria meningitidis OMPC and 225 mcg of aluminum as amorphous aluminum hydroxyphosphate sulfate (previously referred to as aluminum hydroxide), in 0.9% sodium chloride, but does not contain lactose or thimerosal. Liquid PedvaxHIB is a slightly opaque white suspension.

This vaccine is for intramuscular administration and not for intravenous injection. (See DOSAGE AND ADMINISTRATION.)

CLINICAL PHARMACOLOGY

Prior to the introduction of Haemophilus b Conjugate Vaccines, Haemophilus influenzae type b (Hib) was the most frequent cause of bacterial meningitis and a leading cause of serious, systemic bacterial disease in young children worldwide.{1,2,3,4}

Hib disease occurred primarily in children under 5 years of age in the United States prior to the initiation of a vaccine program and was estimated to account for nearly 20,000 cases of invasive infections annually, approximately 12,000 of which were meningitis. The mortality rate from Hib meningitis is about 5%. In addition, up to 35% of survivors develop neurologic sequelae including seizures, deafness, and mental retardation.{5,6} Other invasive diseases caused by this bacterium include cellulitis, epiglottitis, sepsis, pneumonia, septic arthritis, osteomyelitis and pericarditis.

Prior to the introduction of the vaccine, it was estimated that 17% of all cases of Hib disease occurred in infants less than 6 months of age.{7} The peak incidence of Hib meningitis occurs between 6 to 11 months of age. Forty-seven percent of all cases occur by one year of age with the remaining 53% of cases occurring over the next four years.{2,20}

Among children under 5 years of age, the risk of invasive Hib disease is increased in certain populations including the following:

- Daycare attendees{8,9}
- Lower socio-economic groups{10}
- Blacks{11} (especially those who lack the Km(1) immunoglobulin allotype){12}
- Caucasians who lack the G2m(n or 23) immunoglobulin allotype{13}
- Native Americans{14,15,16}
- Household contacts of cases{17}
- Individuals with asplenia, sickle cell disease, or antibody deficiency syndromes{18,19}

An important virulence factor of the Hib bacterium is its polysaccharide capsule (PRP). Antibody to PRP (anti-PRP) has been shown to correlate with protection against Hib disease.{3,21} While the anti-PRP level associated with protection using conjugated vaccines has not yet been determined, the level of anti-PRP associated with protection in studies using bacterial polysaccharide immune globulin or nonconjugated PRP vaccines ranged from >0.15 to >1.0 mcg/mL.{22-28}

Nonconjugated PRP vaccines are capable of stimulating B-lymphocytes to produce antibody without the help of T-lymphocytes (T-independent). The responses to many other antigens are augmented by helper T-lymphocytes (T-dependent). PedvaxHIB is a PRP-conjugate vaccine in which the PRP is covalently bound to the OMPC carrier{29} producing an antigen which is postulated to convert the T-independent antigen (PRP alone) into a T-dependent antigen resulting in both an enhanced antibody response and immunologic memory.

Clinical Evaluation of PedvaxHIB

PedvaxHIB, in a lyophilized formulation (lyophilized PedvaxHIB), was initially evaluated in 3,486 Native American (Navajo) infants, who completed the primary two-dose regimen in a randomized, double-blind, placebo-controlled study (The Protective Efficacy Study). At the time of the study, this population had a much higher incidence of Hib disease than the United States population as a whole and also had a lower antibody response to Haemophilus b Conjugate Vaccines, including PedvaxHIB.{14,15,16,30,33}

Each infant in this study received two doses of either placebo or lyophilized PedvaxHIB with the first dose administered at a mean of 8 weeks of age and the second administered approximately two months later; DTP and OPV were administered concomitantly. Antibody levels were measured in a subset of each group (TABLE 1).

TABLE 1: Antibody Responses in Navajo Infants
Vaccine | No. of Subjects | Time | % Subjects with |  | Anti-PRP GMT (mcg/mL)
Vaccine | No. of Subjects | Time | >0.15 mcg/mL | >1.0 mcg/mL | Anti-PRP GMT (mcg/mL)
Lyophilized PedvaxHIB [Post-Vaccination values obtained approximately 1–3 months after each dose.] | 416 [The Protective Efficacy Study] | Pre-Vaccination | 44 | 10 | 0.16
Lyophilized PedvaxHIB [Post-Vaccination values obtained approximately 1–3 months after each dose.] | 416 | Post-Dose 1 | 88 | 52 | 0.95
Lyophilized PedvaxHIB [Post-Vaccination values obtained approximately 1–3 months after each dose.] | 416 | Post-Dose 2 | 91 | 60 | 1.43
Placebo | 461 | Pre-Vaccination | 44 | 9 | 0.16
Placebo | 461 | Post-Dose 1 | 21 | 2 | 0.09
Placebo | 461 | Post-Dose 2 | 14 | 1 | 0.08
Lyophilized PedvaxHIB | 27 [Immunogenicity Trial{34}] | Prebooster | 70 | 33 | 0.51
Lyophilized PedvaxHIB | 27 | Postbooster [Booster given at 12 months of age; Post-Vaccination values obtained 1 month after administration of booster dose.] | 100 | 89 | 8.39

Most subjects were initially followed until 15 to 18 months of age. During this time, 22 cases of invasive Hib disease occurred in the placebo group (8 cases after the first dose and 14 cases after the second dose) and only 1 case in the vaccine group (none after the first dose and 1 after the second dose). Following the primary two-dose regimen, the protective efficacy of lyophilized PedvaxHIB was calculated to be 93% with a 95% confidence interval of 57%-98% (p=0.001, two-tailed). In the two months between the first and second doses, the difference in number of cases of disease between placebo and vaccine recipients (8 vs. 0 cases, respectively) was statistically significant (p=0.008, two-tailed); however, a primary two-dose regimen is required for infants 2-14 months of age.

At termination of the study, placebo recipients were offered vaccine. All original participants were then followed two years and nine months from termination of the study. During this extended follow-up, invasive Hib disease occurred in an additional seven of the original placebo recipients prior to receiving vaccine and in one of the original vaccine recipients (who had received only one dose of vaccine). No cases of invasive Hib disease were observed in placebo recipients after they received at least one dose of vaccine. Efficacy for this follow-up period, estimated from person-days at risk, was 96.6% (95 C.I., 72.2-99.9%) in children under 18 months of age and 100% (95 C.I., 23.5-100%) in children over 18 months of age.{33}

Since protective efficacy with lyophilized PedvaxHIB was demonstrated in such a high risk population, it would be expected to be predictive of efficacy in other populations.

The safety and immunogenicity of lyophilized PedvaxHIB were evaluated in infants and children in other clinical studies that were conducted in various locations throughout the United States. PedvaxHIB was highly immunogenic in all age groups studied.{31,32}

Lyophilized PedvaxHIB induced antibody levels greater than 1.0 mcg/mL in children who were poor responders to nonconjugated PRP vaccines. In a study involving such a subpopulation,{33,34} 34 children ranging in age from 27 to 61 months who developed invasive Hib disease despite previous vaccination with nonconjugated PRP vaccines were randomly assigned to 2 groups. One group (n=14) was vaccinated with lyophilized PedvaxHIB and the other group (n=20) with a nonconjugated PRP vaccine at a mean interval of approximately 12 months after recovery from disease. All 14 children vaccinated with lyophilized PedvaxHIB but only 6 of 20 children re-vaccinated with a nonconjugated PRP vaccine achieved an antibody level of >1.0 mcg/mL. The 14 children who had not responded to revaccination with the nonconjugated PRP vaccine were then vaccinated with a single dose of lyophilized PedvaxHIB; following this vaccination, all achieved antibody levels of >1.0 mcg/mL.

In addition, lyophilized PedvaxHIB has been studied in children at high risk of Hib disease because of genetically-related deficiencies [Blacks who were Km(1) allotype negative and Caucasians who were G2m(23) allotype negative] and are considered hyporesponsive to nonconjugated PRP vaccines on this basis.{35} The hyporesponsive children had anti-PRP responses comparable to those of allotype positive children of similar age range when vaccinated with lyophilized PedvaxHIB. All children achieved anti-PRP levels of >1.0 mcg/mL.

The safety and immunogenicity of Liquid PedvaxHIB were compared with those of lyophilized PedvaxHIB in a randomized clinical study involving 903 infants 2 to 6 months of age from the general U.S. population. DTP and OPV were administered concomitantly to most subjects. The antibody responses induced by each formulation of PedvaxHIB were similar. TABLE 2 shows antibody responses from this clinical study in subjects who received their first dose at 2 to 3 months of age.

TABLE 2: Antibody Responses to Liquid and Lyophilized PedvaxHIB in Infants From the General U.S. Population
Formulation | Age (Months) | Time | No. of Subjects | % Subjects with anti-PRP |  | Anti-PRP GMT (mcg/mL)
Formulation | Age (Months) | Time | No. of Subjects | >0.15 mcg/mL | >1.0 mcg/mL | Anti-PRP GMT (mcg/mL)
Liquid PedvaxHIB (7.5 mcg PRP) |  | Pre-Vaccination | 487 | 32 | 7 | 0.12
Liquid PedvaxHIB (7.5 mcg PRP) | 2-3 | Post-Dose 1 [Approximately two months Post-Vaccination] | 480 | 94 | 64 | 1.55
Liquid PedvaxHIB (7.5 mcg PRP) |  | Post-Dose 2 [Approximately one month Post-Vaccination] | 393 | 97 | 80 | 3.22
Liquid PedvaxHIB (7.5 mcg PRP) | 12-15 | Prebooster | 284 | 80 | 30 | 0.49
 |  | Postbooster | 284 | 99 | 95 | 10.23
 | 24 [Approximately] | Persistence | 94 | 97 | 55 | 1.29
Lyophilized PedvaxHIB (15 mcg PRP) |  | Pre-Vaccination | 171 | 37 | 6 | 0.13
Lyophilized PedvaxHIB (15 mcg PRP) | 2-3 | Post-Dose 1 | 169 | 97 | 72 | 1.88
Lyophilized PedvaxHIB (15 mcg PRP) |  | Post-Dose 2 | 133 | 99 | 81 | 2.69
Lyophilized PedvaxHIB (15 mcg PRP) | 12-15 | Prebooster | 87 | 71 | 28 | 0.39
 |  | Postbooster | 87 | 99 | 91 | 7.64
 | 24 | Persistence | 37 | 97 | 54 | 1.10

A booster dose of PedvaxHIB is required in infants who complete the primary two-dose regimen before 12 months of age. This booster dose will help maintain antibody levels during the first two years of life when children are at highest risk for invasive Hib disease. (See TABLE 2 and DOSAGE AND ADMINISTRATION.)

In four United States studies, antibody responses to lyophilized PedvaxHIB were evaluated in several subpopulations of infants initially vaccinated between 2 to 3 months of age. (See TABLE 3.)

TABLE 3: Antibody Responses [One month after the second dose] After Two Doses of Lyophilized PedvaxHIB Among Infants Initially Vaccinated at 2–3 Months of Age By Racial/Ethnic Group
LYOPHILIZED
Racial/Ethnic Groups | No. of Subjects | % Subjects With Anti-PRP |  | Anti-PRP GMT (mcg/mL)
Racial/Ethnic Groups | No. of Subjects | >0.15 mcg/mL | >1.0 mcg/mL | Anti-PRP GMT (mcg/mL)
Native American [Apache and Navajo] | 54 | 96 | 70 | 2.47
Caucasian | 201 | 99 | 82 | 3.52
Hispanic | 76 | 99 | 88 | 3.54
Black | 23 | 100 | 96 | 5.40

In two United States studies, antibody responses to Liquid PedvaxHIB were evaluated in several subpopulations of infants initially vaccinated between 2 to 3 months of age. (See TABLE 4.)

TABLE 4: Antibody Responses [One month after the second dose] After Two Doses of Liquid PedvaxHIB Among Infants Initially Vaccinated at 2–3 Months of Age By Racial/Ethnic Group
LIQUID
Racial/Ethnic Groups | No. of Subjects | % Subjects With Anti-PRP |  | Anti-PRP GMT (mcg/mL)
Racial/Ethnic Groups | No. of Subjects | >0.15 mcg/mL | >1.0 mcg/mL | Anti-PRP GMT (mcg/mL)
Native American [Apache and Navajo] | 90 | 97 | 78 | 2.76
Caucasian | 143 | 94 | 72 | 2.16
Hispanic | 184 | 98 | 85 | 4.34
Black | 18 | 100 | 94 | 7.58

Antibodies to the OMPC of N. meningitidis have been demonstrated in vaccinee sera, but the clinical relevance of these antibodies has not been established.{33}

Interchangeability of Licensed Haemophilus b Conjugate Vaccines and PedvaxHIB

Published studies have examined the interchangeability of other licensed Haemophilus b Conjugate Vaccines and PedvaxHIB.{42,43,44,45,52} According to the American Academy of Pediatrics, excellent immune responses have been achieved when different vaccines have been interchanged in the primary series. If PedvaxHIB is given in a series with one of the other products licensed for infants, the recommended number of doses to complete the series is determined by the other product and not by PedvaxHIB. PedvaxHIB may be interchanged with other licensed Haemophilus b Conjugate Vaccines for the booster dose.{52}

Use with Other Vaccines

Results from clinical studies indicate that Liquid PedvaxHIB can be administered concomitantly with DTP, OPV, eIPV (enhanced inactivated poliovirus vaccine), VARIVAX® [Varicella Virus Vaccine Live (Oka/Merck)], M-M-R® II (Measles, Mumps, and Rubella Virus Vaccine Live) or RECOMBIVAX HB® [Hepatitis B Vaccine (Recombinant)].{33} No impairment of immune response to individual tested vaccine antigens was demonstrated.

The type, frequency and severity of adverse experiences observed in these studies with PedvaxHIB were similar to those seen when the other vaccines were given alone.

In addition, a PRP-OMPC-containing product, COMVAX® [Haemophilus b Conjugate (Meningococcal Protein Conjugate) and Hepatitis B (Recombinant) Vaccine], was given concomitantly with a booster dose of DTaP [diphtheria, tetanus, acellular pertussis] at approximately 15 months of age, using separate sites and syringes for injectable vaccines. No impairment of immune response to these individually tested vaccine antigens was demonstrated. COMVAX has also been administered concomitantly with the primary series of DTaP to a limited number of infants. PRP antibody responses are satisfactory for COMVAX, but immune responses are currently unavailable for DTaP (see Manufacturer's Product Circular for COMVAX). No serious vaccine-related adverse events were reported.{33}

INDICATIONS AND USAGE

Liquid PedvaxHIB is indicated for routine vaccination against invasive disease caused by Haemophilus influenzae type b in infants and children 2 to 71 months of age.

Liquid PedvaxHIB will not protect against disease caused by Haemophilus influenzae other than type b or against other microorganisms that cause invasive disease such as meningitis or sepsis. As with any vaccine, vaccination with Liquid PedvaxHIB may not result in a protective antibody response in all individuals given the vaccine.

BECAUSE OF THE POTENTIAL FOR IMMUNE TOLERANCE, Liquid PedvaxHIB IS NOT RECOMMENDED FOR USE IN INFANTS YOUNGER THAN 6 WEEKS OF AGE. (See PRECAUTIONS.)

Revaccination

Infants completing the primary two-dose regimen before 12 months of age should receive a booster dose (see DOSAGE AND ADMINISTRATION).

CONTRAINDICATIONS

Hypersensitivity to any component of the vaccine or the diluent.

Persons who develop symptoms suggestive of hypersensitivity after an injection should not receive further injections of the vaccine.

PRECAUTIONS

General

As for any vaccine, adequate treatment provisions, including epinephrine, should be available for immediate use should an anaphylactoid reaction occur.

Use caution when vaccinating latex-sensitive individuals since the vial stopper contains dry natural latex rubber that may cause allergic reactions.

Special care should be taken to ensure that the injection does not enter a blood vessel.

It is important to use a separate sterile syringe and needle for each patient to prevent transmission of hepatitis B or other infectious agents from one person to another.

As with other vaccines, Liquid PedvaxHIB may not induce protective antibody levels immediately following vaccination.

As reported with Haemophilus b Polysaccharide Vaccine{36} and another Haemophilus b Conjugate Vaccine{37}, cases of Hib disease may occur in the week after vaccination, prior to the onset of the protective effects of the vaccines.

There is insufficient evidence that Liquid PedvaxHIB given immediately after exposure to natural Haemophilus influenzae type b will prevent illness.

The decision to administer or delay vaccination because of current or recent febrile illness depends on the severity of symptoms and on the etiology of the disease. The Advisory Committee on Immunization Practices (ACIP) has recommended that vaccination should be delayed during the course of an acute febrile illness. All vaccines can be administered to persons with minor illnesses such as diarrhea, mild upper-respiratory infection with or without low-grade fever, or other low-grade febrile illness. Persons with moderate or severe febrile illness should be vaccinated as soon as they have recovered from the acute phase of the illness.{46}

If PedvaxHIB is used in persons with malignancies or those receiving immunosuppressive therapy or who are otherwise immunocompromised, the expected immune response may not be obtained.

Instructions to Healthcare Provider

The healthcare provider should determine the current health status and previous vaccination history of the vaccinee.

The healthcare provider should question the patient, parent, or guardian about reactions to a previous dose of PedvaxHIB or other Haemophilus b Conjugate Vaccines.

Information for Patients

The healthcare provider should provide the vaccine information required to be given with each vaccination to the patient, parent, or guardian.

The healthcare provider should inform the patient, parent, or guardian of the benefits and risks associated with vaccination. For risks associated with vaccination, see ADVERSE REACTIONS.

Patients, parents, and guardians should be instructed to report any serious adverse reactions to their healthcare provider who in turn should report such events to the U. S. Department of Health and Human Services through the Vaccine Adverse Event Reporting System (VAERS), 1-800-822-7967.{47}

Laboratory Test Interactions

Sensitive tests (e.g., Latex Agglutination Kits) may detect PRP derived from the vaccine in urine of some vaccinees for at least 30 days following vaccination with lyophilized PedvaxHIB;{38} in clinical studies with lyophilized PedvaxHIB, such children demonstrated normal immune response to the vaccine.

Carcinogenesis, Mutagenesis, Impairment of Fertility

Liquid PedvaxHIB has not been evaluated for carcinogenic or mutagenic potential, or potential to impair fertility.

Pregnancy

Animal reproduction studies have not been conducted with PedvaxHIB. Liquid PedvaxHIB is not recommended for use in individuals 6 years of age and older.

Pediatric Use

Safety and effectiveness in infants below the age of 2 months and in children 6 years of age and older have not been established. In addition, Liquid PedvaxHIB should not be used in infants younger than 6 weeks of age because this will lead to a reduced anti-PRP response and may lead to immune tolerance (impaired ability to respond to subsequent exposure to the PRP antigen).{49-51} Liquid PedvaxHIB is not recommended for use in individuals 6 years of age and older because they are generally not at risk of Hib disease.

Geriatric Use

This vaccine is NOT recommended for use in adult populations.

ADVERSE REACTIONS

Liquid PedvaxHIB

In a multicenter clinical study (n=903) comparing the effects of Liquid PedvaxHIB with those of lyophilized PedvaxHIB, 1,699 doses of Liquid PedvaxHIB were administered to 678 healthy infants 2 to 6 months of age from the general U.S. population. DTP and OPV were administered concomitantly to most subjects. Both formulations of PedvaxHIB were generally well tolerated and no serious vaccine-related adverse reactions were reported.

During a three-day period following primary vaccination with Liquid PedvaxHIB in these infants, the most frequently reported (>1%) adverse reactions, without regard to causality, excluding those shown in TABLE 5, in decreasing order of frequency, were: irritability, sleepiness, injection site pain/soreness, injection site erythema (≤2.5 cm diameter, see also TABLE 5), injection site swelling/induration (≤2.5 cm diameter, see also TABLE 5), unusual high-pitched crying, prolonged crying (>4 hr), diarrhea, vomiting, crying, pain, otitis media, rash, and upper respiratory infection.

Selected objective observations reported by parents over a 48-hour period in these infants following primary vaccination with Liquid PedvaxHIB are summarized in TABLE 5.

TABLE 5: Fever or Local Reactions in Subjects First Vaccinated at 2 to 6 Months of Age with Liquid PedvaxHIB [DTP and OPV were administered concomitantly to most subjects.]
 |  | Post-Dose 1 (hr) |  |  |  | Post-Dose 2 (hr)
Reaction | No. of Subjects Evaluated | 6 | 24 | 48 | No. of Subjects Evaluated | 6 | 24 | 48
 |  | Percentage |  |  |  | Percentage
Fever [Fever was also measured by another method or reported as normal for an additional 345 infants after dose 1 and for an additional 249 infants after dose 2; however, these data are not included in this table.] >38.3°C (≥101°F) Rectal | 222 | 18.1 | 4.4 | 0.5 | 206 | 14.1 | 9.4 | 2.8
Erythema >2.5 cm diameter | 674 | 2.2 | 1.0 | 0.5 | 562 | 1.6 | 1.1 | 0.4
Swelling >2.5 cm diameter | 674 | 2.5 | 1.9 | 0.9 | 562 | 0.9 | 0.9 | 1.3

Adverse reactions during a three-day period following administration of the booster dose were generally similar in type and frequency to those seen following primary vaccination.

Lyophilized PedvaxHIB

In The Protective Efficacy Study (see CLINICAL PHARMACOLOGY), 4,459 healthy Navajo infants 6 to 12 weeks of age received lyophilized PedvaxHIB or placebo. Most of these infants received DTP/OPV concomitantly. No differences were seen in the type and frequency of serious health problems expected in this Navajo population or in serious adverse experiences reported among those who received lyophilized PedvaxHIB and those who received placebo, and none was reported to be related to lyophilized PedvaxHIB. Only one serious reaction (tracheitis) was reported as possibly related to lyophilized PedvaxHIB and only one (diarrhea) as possibly related to placebo. Seizures occurred infrequently in both groups (9 occurred in vaccine recipients, 8 of whom also received DTP; 8 occurred in placebo recipients, 7 of whom also received DTP) and were not reported to be related to lyophilized PedvaxHIB.

In early clinical studies involving the administration of 8,086 doses of lyophilized PedvaxHIB alone to 5,027 healthy infants and children 2 months to 71 months of age, lyophilized PedvaxHIB was generally well tolerated. No serious adverse reactions were reported. In a subset of these infants, urticaria was reported in two children, and thrombocytopenia was seen in one child. A cause and effect relationship between these side effects and the vaccination has not been established.

Potential Adverse Reactions

The use of Haemophilus b Polysaccharide Vaccines and another Haemophilus b Conjugate Vaccine has been associated with the following additional adverse effects: early onset Hib disease and Guillain-Barré syndrome. A cause and effect relationship between these side effects and the vaccination was not established.{36,37,39,40,41,49}

Post-Marketing Adverse Reactions

The following additional adverse reactions have been reported with the use of the lyophilized and liquid formulations of PedvaxHIB:

Hemic and Lymphatic System

Lymphadenopathy

Hypersensitivity

Rarely, angioedema

Nervous System

Febrile seizures

Skin

Sterile injection site abscess

DOSAGE AND ADMINISTRATION

Liquid PedvaxHIB

FOR INTRAMUSCULAR ADMINISTRATION

DO NOT INJECT INTRAVENOUSLY

If there is an interruption or delay between doses in the primary series, there is no need to repeat the series, but dosing should be continued at the next clinic visit. (See CONTRAINDICATIONS and PRECAUTIONS.)

2 to 14 Months of Age

Infants 2 to 14 months of age should receive a 0.5 mL dose of vaccine ideally beginning at 2 months of age followed by a 0.5 mL dose 2 months later (or as soon as possible thereafter). When the primary two-dose regimen is completed before 12 months of age, a booster dose is required (see below and TABLE 6). Infants born prematurely, regardless of birth weight, should be vaccinated at the same chronological age and according to the same schedule and precautions as full-term infants and children.{46}

15 Months of Age and Older

Children 15 months of age and older previously unvaccinated against Hib disease should receive a single 0.5 mL dose of vaccine.

Booster Dose

In infants completing the primary two-dose regimen before 12 months of age, a booster dose (0.5 mL) should be administered at 12 to 15 months of age, but not earlier than 2 months after the second dose.

Vaccination regimens for Liquid PedvaxHIB by age group are outlined in TABLE 6.

TABLE 6: Vaccination Regimens for Liquid PedvaxHIB By Age Groups
Age (Months) at First Dose | Primary | Age (Months) at Booster Dose
2–10 | 2 doses, 2 mo. apart | 12–15
11–14 | 2 doses, 2 mo. apart | —
15–71 | 1 dose | —

Interchangeability

PedvaxHIB may be interchanged with other licensed Haemophilus b Conjugate Vaccines for the primary and booster doses.{52} (See CLINICAL PHARMACOLOGY.)

Use with Other Vaccines

Results from clinical studies indicate that Liquid PedvaxHIB can be administered concomitantly with DTP, OPV, eIPV (enhanced inactivated poliovirus vaccine), VARIVAX [Varicella Virus Vaccine Live (Oka/Merck)], M-M-R II (Measles, Mumps, and Rubella Virus Vaccine Live) or RECOMBIVAX HB [Hepatitis B Vaccine (Recombinant)]. No impairment of immune response to these individually tested vaccine antigens was demonstrated.

The type, frequency and severity of adverse experiences observed in these studies with PedvaxHIB were similar to those seen with the other vaccines when given alone. (See CLINICAL PHARMACOLOGY.)

In addition, a PRP-OMPC-containing product, COMVAX [Haemophilus b Conjugate (Meningococcal Protein Conjugate) and Hepatitis B (Recombinant) Vaccine], was given concomitantly with a booster dose of DTaP [diphtheria, tetanus, acellular pertussis] at approximately 15 months of age, using separate sites and syringes for injectable vaccines. No impairment of immune response to these individually tested vaccine antigens was demonstrated. COMVAX has also been administered concomitantly with the primary series of DTaP to a limited number of infants. PRP antibody responses are satisfactory for COMVAX, but immune responses are currently unavailable for DTaP (see Manufacturer's Product Circular for COMVAX). No serious vaccine-related adverse events were reported.{33}

Parenteral drug products should be inspected visually for extraneous particulate matter and discoloration prior to administration whenever solution and container permit.

Liquid PedvaxHIB is a slightly opaque white suspension. (See DESCRIPTION.)

The vaccine should be used as supplied; no reconstitution is necessary.

Shake well before withdrawal and use. Thorough agitation is necessary to maintain suspension of the vaccine.

Inject 0.5 mL intramuscularly, preferably into the anterolateral thigh or the outer aspect of the upper arm. The buttocks should not be used for active vaccination of infants and children, because of the potential risk of injury to the sciatic nerve. Discard vial after use.

HOW SUPPLIED

Liquid PedvaxHIB is supplied as follows:

No. 4897 — A box of 10 single-dose vials of liquid vaccine, NDC 0006-4897-00.

Storage

Store vaccine at 2-8°C (36-46°F).

DO NOT FREEZE.

REFERENCES

1. Cochi, S. L., et al: Immunization of U.S. children with Haemophilus influenzae type b polysaccharide vaccine: A cost-effectiveness model of strategy assessment. JAMA 253: 521-529, 1985.
2. Schlech, W. F., III, et al: Bacterial meningitis in the United States, 1978 through 1981. The National Bacterial Meningitis Surveillance Study. JAMA 253: 1749-1754, 1985.
3. Peltola, H., et al: Prevention of Haemophilus influenzae type b bacteremic infections with the capsular polysaccharide vaccine. N Engl J Med 310: 1561-1566, 1984.
4. Cadoz, M., et al: Etude epidemiologique des cas de meningitis purulentes hospitalises a Dakar pendant la decemie 1970-1979. Bull WHO 59: 575-584, 1981.
5. Sell, S. H., et al: Long-term Sequelae of Haemophilus influenzae meningitis. Pediatr 49: 206-217, 1972.
6. Taylor, H. G., et al: Intellectual, neuropsychological, and achievement outcomes in children six to eight years after recovery from Haemophilus influenzae meningitis. Pediatr 74: 198-205, 1984.
7. Hay, J. W., et al: Cost-benefit analysis of two strategies for prevention of Haemophilus influenzae type b infection. Pediatr 80(3): 319-329, 1987.
8. Redmond, S. R., et al: Haemophilus influenzae type b disease: an epidemiologic study with special reference to daycare centers. JAMA 252: 2581-2584, 1984.
9. Istre, G. R., et al: Risk factors for primary invasive Haemophilus influenzae disease: increased risk from daycare attendance and school age household members. J Pediatr 106: 190-195, 1985.
10. Fraser, D.W., et al: Risk factors in bacterial meningitis: Charleston County, South Carolina. J Infect Dis 127: 271-277, 1973.
11. Tarr, P. I., et al: Demographic factors in the epidemiology of Haemophilus influenzae meningitis in young children. J Pediatr 92: 884-888, 1978.
12. Granoff, D. M., et al: Response to immunization with Haemophilus influenzae type b polysaccharide-pertussis vaccine and risk of Haemophilus meningitis in children with Km(1) immunoglobulin allotype. J Clin Invest 74: 1708-1714, 1984.
13. Ambrosino, D. M., et al: Correlation between G2m(n) immunoglobulin allotype and human antibody response and susceptibility to polysaccharide encapsulated bacteria. J Clin Invest 75: 1935-1942, 1985.
14. Coulehan, J. L., et al: Epidemiology of Haemophilus influenzae type b disease among Navajo Indians. Pub Health Rep 99: 404-409, 1984.
15. Losonsky, G. A., et al: Haemophilus influenzae disease in the White Mountain Apaches: molecular epidemiology of a high risk population. Pediatr Infect Dis J 3: 539-547, 1985.
16. Ward, J. I., et al: Haemophilus influenzae disease in Alaskan Eskimos: characteristics of a population with an unusual incidence of disease. Lancet 1: 1281-1285, 1981.
17. Ward, J. I., et al: Haemophilus influenzae meningitis: a national study of secondary spread in household contacts. N Engl J Med 301: 122-126, 1979.
18. Ward, J., et al: Haemophilus influenzae bacteremia in children with sickle cell disease. J Pediatr 88: 261-263, 1976.
19. Bartlett, A. V., et al: Unusual presentations of Haemophilus influenzae infections in immunocompromised patients. J Pediatr 102: 55-58, 1983.
20. Recommendations of the Immunization Practices Advisory Committee. Polysaccharide vaccine for prevention of Haemophilus influenzae type b disease. MMWR 34(15): 201-205, 1985.
21. Santosham, M., et al: Prevention of Haemophilus influenzae type b infections in high-risk infants treated with bacterial polysaccharide immune globulin. N Engl J Med 317: 923-929, 1987.
22. Siber, G. R., et al: Preparation of human hyperimmune globulin to Haemophilus influenzae b, Streptococcus pneumoniae, and Neisseria meningitidis. Infect Immun 45: 248-254, 1984.
23. Smith, D. H., et al: Responses of children immunized with the capsular polysaccharide of Haemophilus influenzae type b. Pediatr 52: 637-645, 1973.
24. Robbins, J. B., et al: Quantitative measurement of 'natural' and immunization-induced Haemophilus influenzae type b capsular polysaccharide antibodies. Pediatr Res 7: 103-110, 1973.
25. Kaythy, H., et al: The protective level of serum antibodies to the capsular polysaccharide of Haemophilus influenzae type b. J Infect Dis 147: 1100, 1983.
26. Peltola, H., et al: Haemophilus influenzae type b capsular polysaccharide vaccine in children: a double-blind field study of 100,000 vaccinees 3 months to 5 years of age in Finland. Pediatr 60: 730-737, 1977.
27. Ward, J. I., et al: Haemophilus influenzae type b vaccines: Lessons For the Future. Pediatr 81: 886-893, 1988.
28. Daum, R. S., et al: Haemophilus influenzae type b vaccines: Lessons From the Past. Pediatr 81: 893-897, 1988.
29. Marburg, S., et al: Bimolecular chemistry of macromolecules: Synthesis of bacterial polysaccharide conjugates with Neisseria meningitidis membrane protein. J Am Chem Soc 108: 5282-5287, 1986.
30. Letson, G. W., et al: Comparison of active and combined passive/active immunization of Navajo children against Haemophilus influenzae type b. Pediatr Infect Dis J 7(111): 747-752, 1988.
31. Einhorn, M. S., et al: Immunogenicity in infants of Haemophilus influenzae type b polysaccharide in a conjugate vaccine with Neisseria meningitidis outer-membrane protein. Lancet 2: 299-302, 1986.
32. Ahonkhai, V.I., et al: Haemophilus influenzae type b Conjugate Vaccine (Meningococcal Protein Conjugate) (PedvaxHIB TM): Clinical Evaluation. Pediatr 85(4): 676-681, 1990.
33. Data on file at Research Laboratories of Merck Sharp & Dohme LLC, Rahway, NJ, USA.
34. Granoff, D. M., et al: Immunogenicity of Haemophilus influenzae type b polysaccharide—outer membrane protein conjugate vaccine in patients who acquired Haemophilus disease despite previous vaccination with type b polysaccharide vaccine. J. Pediatr. 114(6): 925-933, June 1989.
35. Lenoir, A. A., et al: Response to Haemophilus influenzae type b (H. influenzae type b) polysaccharide N. meningitidis outer membrane protein (PS-OMP) conjugate vaccine in relation to Km(1) and G2m(23) allotypes. Twenty-sixth Interscience Conference on Antimicrobial Agents and Chemotherapy (Abstract #216) 133, 1986.
36. Mortimer, E. A.: Efficacy of Haemophilus b polysaccharide vaccine: An enigma. JAMA 260: 1454, 1988.
37. Meekison, W., et al: Post-marketing surveillance of adverse effects following ProHIBiT vaccine. British Columbia Canada Diseases Weekly Report 15-28: 143-145, 1989.
38. Goepp, J. G., et al: Persistent urinary antigen excretion in infants vaccinated with Haemophilus influenzae type b capsular polysaccharide conjugated with outer membrane protein from Neisseria meningitidis. Pediatr Infect Dis J 11(1): 2-5, 1992.
39. Milstein, J. B., et al: Adverse reactions reported following receipt of Haemophilus influenzae type b vaccine: An analysis after one year of marketing. Pediatr 80: 270, 1987.
40. Black, S., et al: b-CAPSA 1 Haemophilus influenzae type b capsular polysaccharide vaccine safety. Pediatr 79: 321-325, 1987.
41. D'Cruz, O. F., et al: Acute inflammatory demyelinating polyradiculoneuropathy (Guillain-Barré syndrome) after immunization with Haemophilus influenzae type b Conjugate Vaccine. J Pediatr 115: 743-746, 1989.
42. Recommendations of the Immunization Practices Advisory Committee. Recommendations for use of Haemophilus b Conjugate Vaccines and a combined diphtheria, tetanus, pertussis, and Haemophilus b vaccine. MMWR 42(RR-13): 1-15, 1993.
43. Daum, R. S., et al: Interchangeability of Haemophilus influenzae type b vaccines for the primary series (mix and match): a preliminary analysis [Abstract 976]. Pediatr Res 33: 166A, 1993.
44. Greenberg, D. P., et al: Enhanced antibody responses in infants given different sequences of heterogenous Haemophilus influenzae type b Conjugate Vaccines. J Pediatr 126: 206-211, 1995.
45. Anderson, E. L., et al: Interchangeability of Conjugated Haemophilus influenzae type b Vaccines in Infants. JAMA 273: 849-853, 1995.
46. Recommendations of the Immunization Practices Advisory Committee. General Recommendations on Immunization. MMWR 43(RR-1), 1994.
47. Vaccine Adverse Event Reporting System - United States. MMWR 39(41): 730-733, October 19, 1990.
48. Institute of Medicine Adverse Events Associated With Childhood Vaccines Evidence Bearing on Causality. National Academy Press, Washington, D.C., 260-261, 1994.
49. Keyserling, H.L., et al: Program and Abstracts of the 30th ICAAC, (Abstract #63), 1990.
50. Ward, J.I., et al: Program and Abstracts of the 32nd ICAAC, (Abstract #984), 1992.
51. Lieberman, J.M., et al: Infect Dis, (Abstract #1028), 1993.
52. American Academy of Pediatrics. Recommended Childhood Immunization Schedule - United States, January-December 1998. Pediatr 101(1): 154-157, 1998.

Manuf. and Dist. by: Merck Sharp & Dohme LLC
Rahway, NJ 07065, USA

For patent information: www.msd.com/research/patent.

Copyright © 1996-2023 Merck & Co., Inc., Rahway, NJ, USA, and its affiliates.
All rights reserved.

Revised: 04/2023

uspi-v120-i-2304r006

This is a representative sample of the packaging. Please see How Supplied section for a complete list of available packaging.

PRINCIPAL DISPLAY PANEL - 0.5 mL Vial Carton

NDC 0006-4897-00
10 Single-dose
0.5 mL Vials Vaccine

HAEMOPHILUS b CONJUGATE VACCINE
(Meningococcal Protein Conjugate)
Liquid PedvaxHIB®

Each 0.5 mL of vaccine is formulated to contain: 7.5 mcg of Haemophilus influenzae type b
polysaccharide, 125 mcg of Neisseria meningitidis outer membrane protein complex,
225 mcg of amorphous aluminum hydroxyphosphate sulfate in 0.9% sodium chloride.

Rx only